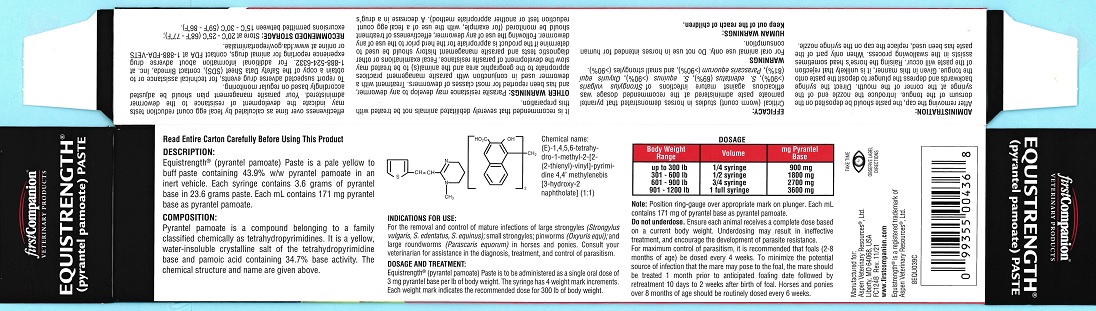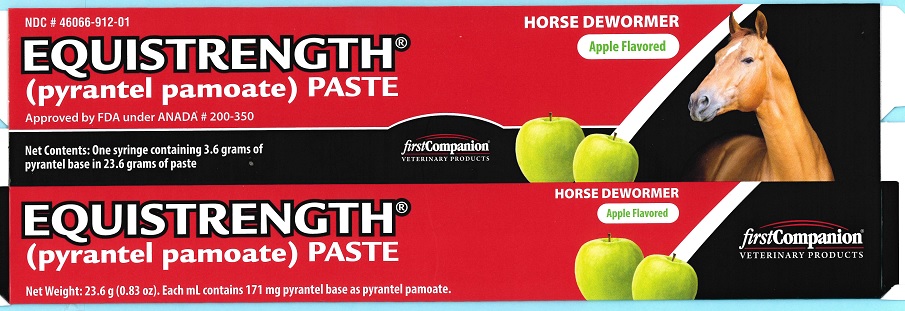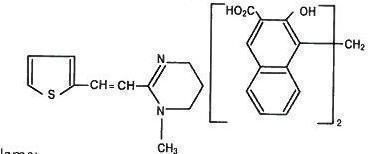 DRUG LABEL: Equistrength
NDC: 46066-912 | Form: PASTE
Manufacturer: Aspen Veterinary
Category: animal | Type: OTC ANIMAL DRUG LABEL
Date: 20231218

ACTIVE INGREDIENTS: PYRANTEL PAMOATE 3.6 g/23.6 g

DESCRIPTION

Read Entire Carton Carefully Before Using This Product

DESCRIPTION:

Equistrength® Paste (pyrantel pamoate) is a pale yellow to buff paste containing 43.9% w/w pyrantel pamoate in an inert vehicle. Each syringe contains 3.6 grams pyrantel base in 23.6 grams paste. Each mL contains 171 mg pyrantel base as pyrantel pamoate.

COMPONENTS

COMPOSITION:

Pyrantel pamoate is a compound belonging to a family classified chemically as tetrahydropyrimidines. It is a yellow, water-insoluble crystalline salt of the tetrahydropyrimidine base and pamoic acid containing 34.7% base activity.

The chemical structure and name are given below:

Chemical Name:

(E)-1,4,5,6-tetrahydro-1-methyl-2-[2-(2-thienyl)-vinyl]-pyrimidine 4,4' methylenebis [3-hydroxy-2 naphtholate] (1:1)

INDICATIONS FOR USE:

For the removal and control of mature infections of large strongyles (Strongylus vulgaris, S. edentatus, S. equinus); small strongyles; pinworms (Oxyuris equi); and large roundworms (Parascaris equorum) in horses and ponies.

Consult your veterinarian for assistance in the diagnosis, treatment, and control of parasitism.

DOSAGE AND TREATMENT:

Equistrength® Paste (pyrantel pamoate) is to be administered as a single oral dose of 3 mg pyrantel base per lb of body weight. The syringe has four weight mark increments. Each weight mark indicates the recommended dose for 300 lb of body weight.

DOSAGE
Body Weight Range | Volume | mg Pyrantel Base
up to 300 lb | 1/4 syringe | 900 mg
301 - 600 lb | 1/2 syringe | 1800 mg
601 - 900 lb | 3/4 syringe | 2700 mg
901 - 1200 lb | 1 full syringe | 3600 mg

Note: Position ring-gauge over appropriate mark on plunger. Each mL contains 171 mg of pyrantel base as pyrantel pamoate.

Do not underdose. Ensure each animal receives a complete dose based on a current body weight. Underdosing may result in ineffective treatment, and encourage the development of parasite resistance.

For maximum control of parasitism, it is recommended that foals (2-8 months of age) be dosed every 4 weeks. To minimize the potential source of infection that the mare may pose to the foal, the mare should be treated 1 month prior to anticipated foaling date followed by re-treatment 10 days to 2 weeks after birth of foal. Horses and ponies over 8 months of age should be routinely dosed every 6 weeks.

ADMINISTRATION:

After removing the cap, the paste should be deposited on the dorsum of the tongue. Introduce the nozzle end of the syringe at the corner of the mouth. Direct the syringe backwards and depress the plunger to deposit the paste onto the tongue. Given in this manner, it is unlikely that rejection of the paste will occur. Raising the horse's head sometimes assists in the swallowing process. When only part of the paste has been used, replace the cap on the syringe nozzle.

SUMMARY OF SAFETY AND EFFECTIVENESS

EFFICACY:

Critical (worm count) studies in horses demonstrated that pyrantel pamoate paste administered at the recommended dosage was efficacious against mature infections of Strongylus vulgaris (>90%), Oxyuris equi (81%), Parascaris equorum (>90%), and small strongyles (>90%).

WARNINGS

For oral animal use only. Do not use in horses intended for human consumption.

HUMAN WARNINGS:

Keep out of the reach of children.

It is recommended that severely debilitated animals not be treated with this preparation.

WARNINGS

OTHER WARNINGS: Parasite resistance may develop to any dewormer, and has been reported for most classes of dewormers. Treatment with a dewormer used in conjunction with parasite management practices appropriate to the geographic area and the animal(s) to be treated may slow the development of parasite resistance. Fecal examinations or other diagnostic tests and parasite management history should be used to determine if the product is appropriate for the herd prior to the use of any dewormer. Following the use of any dewormer, effectiveness of treatment should be monitored (for example, with the use of a fecal egg count reduction test or another appropriate method). A decrease in a drug's effectiveness over time as calculated by fecal egg count reduction tests may indicate the development of resistance to the dewormer administered. Your parasite management plan should be adjusted accordingly based on regular monitoring.

To report suspected adverse drug events, for technical assistance or to obtain a copy of the Safety Data Sheet (SDS), contact Bimeda, Inc. at 1-888-524-6332. For additional information about adverse drug experience reporting for animal drugs, contact FDA at 1-888-FDA-VETS or online at www.fda.gov/reportanimalae.

STORAGE AND HANDLING

RECOMMENDED STORAGE: Store at 20°C-25°C (68°F-77°F); excursions permitted between 15°C-30°C (59°F-86°F).